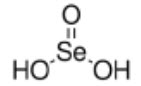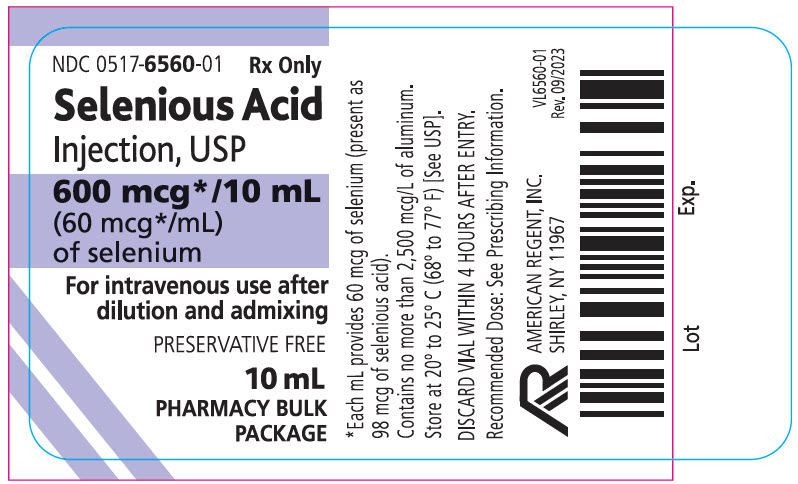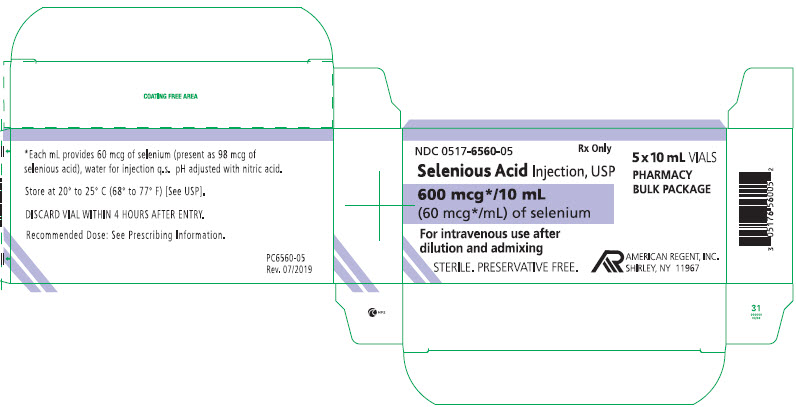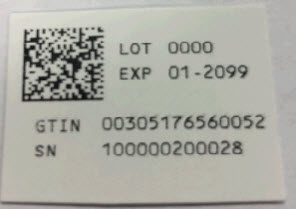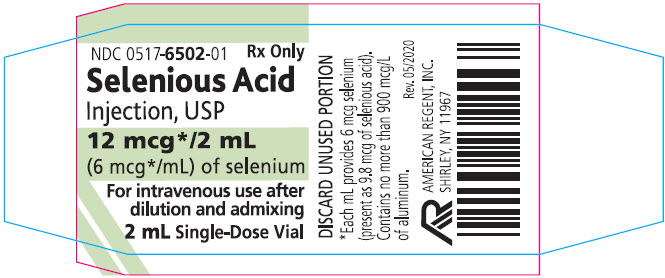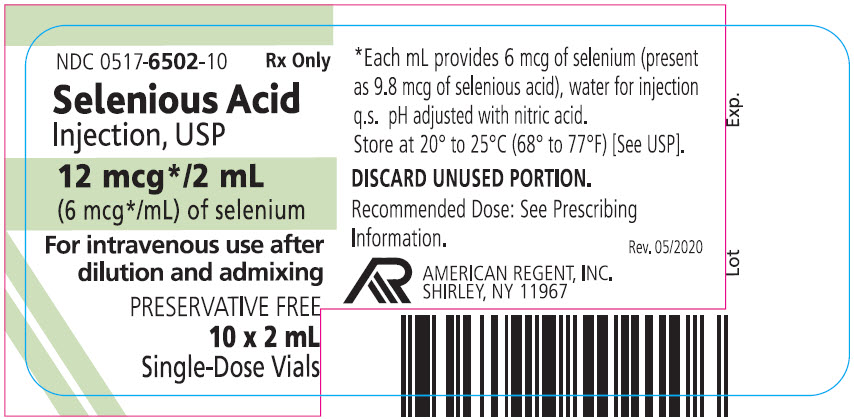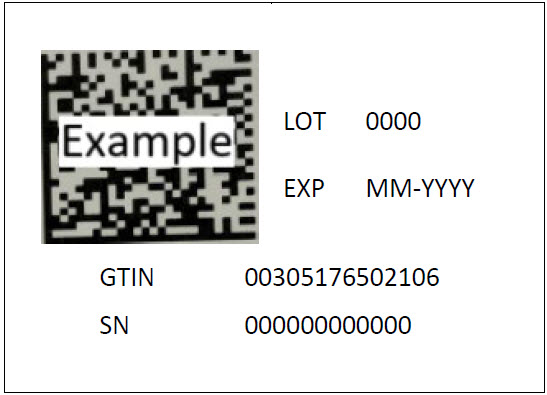 DRUG LABEL: Selenious Acid
NDC: 0517-6560 | Form: INJECTION, SOLUTION
Manufacturer: American Regent, Inc.
Category: prescription | Type: HUMAN PRESCRIPTION DRUG LABEL
Date: 20210801

ACTIVE INGREDIENTS: SELENIUM 60 ug/1 mL
INACTIVE INGREDIENTS: WATER; NITRIC ACID

HIGHLIGHTS OF PRESCRIBING INFORMATION

These highlights do not include all the information needed to use SELENIOUS ACID INJECTION safely and effectively. See full prescribing information for SELENIOUS ACID INJECTION.
SELENIOUS ACID INJECTION, for intravenous use
Initial U.S. Approval: 2019

RECENT MAJOR CHANGES

Dosage and Administration, Preparation Instructions for Admixing Using a Parenteral Nutrition Container (2.3) 10/2020

Recommended Dosage and Monitoring in Adult and Pediatric Patients (2.5) 8/2021

1 INDICATIONS AND USAGE

Selenious Acid Injectionis a trace element indicated in adult and pediatric patients as a source of selenium for parenteral nutrition when oral or enteral nutrition is not possible, insufficient, or contraindicated. (1)

2 DOSAGE AND ADMINISTRATION

• Pharmacy Bulk Package or Single-Dose Vial: Not for direct intravenous infusion. (2.1)

• See full prescribing information for information on preparation, administration, and general dosing considerations. (2.1, 2.2, 2.3, 2.4)

Recommended Dosage (2.5)

• Selenious Acid Injection provides 60 mcg/mL of selenium.

• Selenious Acid Injection in a concentration of 6 mcg/mL is recommended for use in pediatric patients, particularly those weighing 7 kg or less.

• Individualize the dosage based upon the patient’s clinical condition, nutritional requirements, and the contribution of oral or enteral selenium intake. The following dosages are general recommendations intended for most patients. However, based upon clinical requirements, some patients may require a higher dosage:

○ Adults: 60 mcg/day

○ Pediatric Patients 7 kg and above: 2 mcg/kg/day (up to 60 mcg/day)

○ Pediatric Patients less than 7 kg: 2 to 4 mcg/kg/day

• Monitor selenium concentrations during treatment.

3 DOSAGE FORMS AND STRENGTHS

Selenious Acid Injection, USP: (3)

- Pharmacy Bulk Package: 600 mcg/10 mL (60 mcg/mL) of selenium
- Single-Dose Vial: 12 mcg/2 mL (6 mcg/mL) of selenium

4 CONTRAINDICATIONS

None. (4)

5 WARNINGS AND PRECAUTIONS

- Pulmonary Embolism due to Pulmonary Vascular Precipitates: If signs of pulmonary distress occur, stop the infusion and initiate a medical evaluation. (5.1)
- Vein Damage and Thrombosis: Solutions with osmolarity of 900 mOsmol/L or more must be infused through a central venous catheter. (2.1, 5.2)
- Aluminum Toxicity: Increased risk in patients with renal impairment, including preterm infants. (5.3, 5.4)
- Monitoring and Laboratory Tests: Monitor selenium concentrations, fluid and electrolyte status, serum osmolarity, blood glucose, liver and kidney function, blood count and coagulation parameters throughout treatment. (5.4, 2.4)

6 ADVERSE REACTIONS

No selenium-related adverse reactions in patients receiving intravenously administered parenteral nutrition solutions containing selenious acid within the recommended dosage range. (6)
To report SUSPECTED ADVERSE REACTIONS, contact American Regent Inc. at 1-800-734-9236 or FDA at 1-800-FDA-1088 or www.fda.gov/medwatch.

FULL PRESCRIBING INFORMATION

RECENT MAJOR CHANGES

Dosage and Administration, Preparation Instructions for Admixing Using a Parenteral Nutrition Container (2.3) 10/2020

1 INDICATIONS AND USAGE

Selenious Acid Injection is indicated in adult and pediatric patients as a source of selenium for parenteral nutrition when oral or enteral nutrition is not possible, insufficient, or contraindicated.

2 DOSAGE AND ADMINISTRATION

2.1 Important Administration Information

Selenious Acid Injection is supplied as a pharmacy bulk package or single-dose vial for admixing use only. It is not for direct intravenous infusion. Prior to administration, Selenious Acid Injectionmust be transferred to a separate parenteral nutrition container, prepared and used as an admixture in parenteral nutrition solutions.

The Pharmacy Bulk Package vial of Selenious Acid Injection is intended for dispensing of single doses to multiple patients in a pharmacy admixture program.

The final parenteral nutrition solution is for intravenous infusion into a central or peripheral vein. The choice of a central or peripheral venous route should depend on the osmolarity of the final infusate. Solutions with osmolarity of 900 mOsmol/L or greater must be infused through a central venous catheter [see Warnings and Precautions (5.2)].

2.2 Preparation and Administration Instructions

• Selenious Acid Injection is not for direct intravenous infusion. Prior to administration, Selenious Acid Injection must be prepared and used as an admixture inparenteral nutrition solutions.

• Selenious Acid Injection is to be prepared only in a suitable work area such as a laminar flow hood (or an equivalent clean air compounding area). The key factor in the preparation is careful aseptic technique to avoid inadvertent touch contamination during mixing of solutions and addition of other nutrients.

• Visually inspect the prepared parenteral nutrition solution containing Selenious Acid Injection for particulate matter before admixing, after admixing, and prior to administration.

2.3 Preparation Instructions for Admixing Using a Parenteral Nutrition Container

- Inspect Selenious Acid Injection vials for particulate matter.
- Transfer Selenious Acid Injection to the parenteral nutrition solution following the admixture of amino acids, dextrose, lipid (if added), and electrolytes solutions.
- Because additives may be incompatible, evaluate all additions to the parenteral nutrition container for compatibility and stability of the resulting preparation. Consult with pharmacist, if available. Questions about compatibility may be directed to America Regent. If it is deemed advisable to introduce additives to the parenteral nutrition container, use aseptic technique.
- Inspect the final parenteral nutrition containing Selenious Acid Injection to ensure that:
  - Precipitates have not formed during mixing or addition of additives.
  - The admixed emulsion has not separated, if a lipid emulsion has been added. Separation of the admixed emulsion can be visibly identified by a yellowish streaking of the accumulation of yellowish droplets.
- Discard if any precipitates are observed.

Stability and Storage

- Single-dose vial (2 mL): Discard unused portion.
- Pharmacy Bulk Package vial (10 mL): Penetrate vial closure only one time with a suitable sterile transfer device or dispensing set that allows measured dispensing of the content.
- Use Selenious Acid Injection for admixing promptly once the sterile transfer set has been inserted into the Pharmacy Bulk Package container or not more than 4 hours at room temperature (25ºC/77ºF) after the container closure has been penetrated. Discard any remaining drug.
- Use parenteral nutrition solutions containing Selenious Acid Injection promptly after mixing. Any storage of the admixture should be under refrigeration from 2°C to 8°C (36°F to 46°F) and limited to a period of time no longer than 9 days. After removal from refrigeration, use promptly and complete the infusion within 24 hours. Discard any remaining admixture.
- Protect the admixed parenteral nutrition solution from light.

2.4 Dosing Considerations

- The dosage of the final parenteral nutrition containing Selenious Acid Injection must be based on the concentrations of all components in the solution and the recommended daily nutritional requirements [see Dosage and Administration (2.5)]. Consult the prescribing information of all added components to determine the recommended nutritional requirements for dextrose, amino acids and lipid emulsion, as applicable.
- Prior to administration of parenteral nutrition solution containing Selenious Acid Injection, correct severe fluid, electrolyte and acid-base disorders.

2.5 Recommended Dosage and Monitoring in Adults and Pediatric Patients

- There are two dosage strengths for Selenious Acid Injection: 6 mcg/mL and 60 mcg/mL of selenium.
- Selenious Acid Injection in a concentration of 6 mcg/mL is recommended for use in pediatric patients, particularly those weighing 7 kg or less.
- The dosage of Selenious Acid Injection should be individualized based on the patient’s clinical condition, nutritional requirements, and the contribution of oral or enteral selenium intake.
- The dosages in Table 1 are general recommendations intended for most patients. However, based on clinical requirements, some patients may require a higher dosage.

Table 1: Recommended Dosage of Selenious Acid Injection for Adults and Pediatric Patients by Estimated Weight

Population | Recommended Dosage
Adults | 60 mcg/day
Pediatric Patients 7 kg and above | 2 mcg/kg/day (up to 60 mcg/day)
Pediatric Patients less than 7 kg | 2 to 4 mcg/kg/day

- Monitor selenium concentrations during treatment. Selenium concentrations may vary depending on the assay used and the laboratory reference range.

3 DOSAGE FORMS AND STRENGTHS

Selenious Acid Injection, USP is a clear colorless solution available in the following:

- Pharmacy Bulk Package: 600 mcg/10mL (60 mcg/mL) of selenium
- Single-Dose Vial: 12 mcg/2 mL (6 mcg/mL) of selenium

4 CONTRAINDICATIONS

None.

5 WARNINGS AND PRECAUTIONS

5.1 Pulmonary Embolism due to Pulmonary Vascular Precipitates

Pulmonary vascular precipitates causing pulmonary vascular emboli and pulmonary distress have been reported in patients receiving parenteral nutrition. The cause of precipitate formation has not been determined in all cases; however, in some fatal cases, pulmonary emboli occurred as a result of calcium phosphate precipitates. Precipitation has occurred following passage through an in-line filter; in vivo precipitate formation may also have occurred. If signs of pulmonary distress occur, stop the parenteral nutrition infusion and initiate a medical evaluation. In addition to inspection of the solution [see Dosage and Administration (2.2, 2.3)], the infusion set and catheter should also periodically be checked for precipitates.

5.2 Vein Damage and Thrombosis

Selenious Acid Injection has a low pH and must be prepared and used as an admixture in parenteral nutrition solutions. It is not for direct intravenous infusion.

In addition, consider the osmolarity of the final parenteral nutrition solution in determining peripheral versus central administration. Solutions with an osmolarity of 900 mOsmol/L or greater must be infused through a central catheter [see Dosage and Administration (2.1)]. The infusion of hypertonic nutrient injections into a peripheral vein may result in vein irritation, vein damage, and/or thrombosis. The primary complication of peripheral access is venous thrombophlebitis, which manifests as pain, erythema, tenderness or a palpable cord. Remove the catheter as soon as possible, if thrombophlebitis develops.

5.3 Aluminum Toxicity

Selenious Acid Injection contains aluminum that may be toxic.

Aluminum may reach toxic levels with prolonged parenteral administration if kidney function is impaired. Preterm infants are particularly at risk for aluminum toxicity because their kidneys are immature, and they require large amounts of calcium and phosphate solutions, which also contain aluminum.

Patients with impaired kidney function, including preterm neonates, who receive greater than 4 to 5 mcg/kg/day of parenteral aluminum can accumulate aluminum to levels associated with central nervous system and bone toxicity. Tissue loading may occur at even lower rates of administration.

Exposure to aluminum from Selenious Acid Injection is not more than 0.6 mcg/kg/day. When prescribing Selenious Acid Injection for use in parenteral nutrition containing other small volume parenteral products, the total daily patient exposure to aluminum from the admixture should be considered and maintained at no more than 5 mcg/kg/day [see Use in Specific Populations (8.4)].

5.4 Monitoring and Laboratory Tests

Monitor selenium concentrations, fluid and electrolyte status, serum osmolarity, blood glucose, liver and kidney function, blood count and coagulation parameters during treatment [see Dosage and Administration (2.5)].

6 ADVERSE REACTIONS

No selenium-related adverse reactions have been reported in clinical studies or postmarketing reports in patients receiving intravenously administered parenteral nutrition solutions containing selenious acid within the recommended dosage range.

The following adverse reactions associated with use of other components of parenteral nutrition solutions were identified in clinical studies or postmarketing reports. Because some of these reactions were reported voluntarily from a population of uncertain size, it is not always possible to reliably estimate their frequency or establish a causal relationship to drug exposure:

- Pulmonary embolism due to pulmonary vascular precipitates [see Warnings and Precautions (5.1)]
- Vein damage and thrombosis [see Warnings and Precautions (5.2)]
- Aluminum toxicity [see Warnings and Precautions (5.3)]

8 USE IN SPECIFIC POPULATIONS

8.1 Pregnancy

Risk Summary

Administration of the recommended dose of Selenious Acid Injection in parenteral nutrition is not expected to cause major birth defects, miscarriage, or adverse maternal or fetal outcomes. Animal reproduction studies have not been conducted with intravenous selenious acid.

The estimated background risk of major birth defects and miscarriage for the indicated populations are unknown. All pregnancies have a background risk of birth defect, loss, or other adverse outcomes. n the U.S. general population, the estimated background risk of major birth defects and miscarriage in clinically recognized pregnancies is 2 to 4% and 15 to 20%, respectively.

Clinical Considerations

Disease-associated Maternal and/or Embryo-Fetal Risk

Deficiency of trace elements, including selenium, is associated with adverse pregnancy and fetal outcomes. Pregnant women have an increased metabolic demand for trace elements, including selenium. Parenteral nutrition with selenium should be considered if a pregnant woman’s nutritional requirements cannot be fulfilled by oral or enteral intake.

8.2 Lactation

Risk Summary

Selenium is present in human milk. Administration of the approved recommended dose of Selenious Acid Injection in parenteral nutrition is not expected to cause harm to a breastfed infant. There is no information on the effects of selenious acid on milk production. The developmental and health benefits of breastfeeding should be considered along with the mother’s clinical need for Selenious Acid Injection and any potential adverse effects on the breastfed infant from Selenious Acid Injection or from the underlying maternal condition.

8.4 Pediatric Use

Selenious Acid Injection is approved for use in the pediatric population, including neonates, as a source of selenium for parenteral nutrition when oral or enteral nutrition is not possible, insufficient, or contraindicated. Safety and dosing recommendations in pediatric patients are based on clinical experience [see Dosage and Administration (2.5)].

Because of immature renal function, preterm infants receiving prolonged parenteral nutrition treatment with Selenious Acid Injection may be at higher risk of aluminum toxicity [see Warnings and Precautions (5.3)].

8.5 Geriatric Use

Reported clinical experience with intravenous selenious acid has not identified a difference in selenium requirements between elderly and younger patients. In general, dose selection should be individualized based on the patient’s clinical condition, nutritional requirements, and additional nutritional intake provided orally or enterally to the patient.

10 OVERDOSAGE

There are no known cases of overdosage with intravenous selenious acid in parenteral nutrition.

Overdosage has been reported with oral selenium. Available selenium concentrations in these subjects have been reported using various assays and laboratory-based reference ranges over a period of time. Interpret results in the context of current reported ranges.

For oral selenium, the Tolerable Upper Limit (UL) is 400 mcg/day and the No Observed Adverse Effect Level (NOAEL) is 800 mcg/day. The estimated oral bioavailability of selenium is approximately 70%.

Acute Oral Toxicity Effects

Serious adverse events and deaths have been reported with acute oral toxicity, however, there is no clear correlation between the amount ingested, signs and symptoms of toxicity, or selenium blood concentrations.

With severe toxicity, the most common presenting symptoms within a few hours post-ingestion of oral doses greater than 1 gram/day of selenium are gastrointestinal (nausea, vomiting, diarrhea, and abdominal pain), altered mental status, and “garlic” breath odor.

Death from circulatory collapse has been reported after oral ingestion of 5 to 10 grams of selenium. Selenium serum or blood concentrations in fatal cases have been reported in the range of 190 mcg/dL to 3,800 mcg/dL.

Mild to moderate intoxication (myalgia, muscle spasms, and irritability) has been reported in patients with selenium serum or blood concentrations in the range of 41 to 750 mcg/dL.

Chronic Selenosis

Chronic daily exposure to selenium from dietary sources (0.003 to 0.007 grams/day) or oral supplements (0.0016 to 0.25 grams/day) may result in alopecia and nail brittleness. Other signs include gastrointestinal disturbances, skin rash, garlic breath, fatigue, irritability, and nervous system abnormalities including paresthesia and ataxia.

Selenium serum or blood concentrations in patients in China exposed through oral (non-dietary) supplementation were in the range of 32 to 150 mcg/dL.

Management

There is no known antidote for acute selenium toxicity. Management of selenium overdosage is supportive care based on presenting signs and symptoms.

11 DESCRIPTION

Selenious Acid Injection, USP is a sterile, non-pyrogenic, clear, colorless solution intended for use as a trace element and additive to intravenous solutions for parenteral nutrition.

Each 600 mcg/10 mL Pharmacy Bulk Package vial contains 10 mL of selenious acid solution.

Each 6 mcg/mL single-dose vial contains 2 mL of selenious acid solution.

None of the presentations contain preservatives.

Each mL of the 60 mcg/mL strength contains 60 mcg of selenium present as 98 mcg of selenious acid, nitric acid for pH adjustment (1.8 to 2.4), and water for injection q.s.

Each mL of the 6 mcg/mL strength contains 6 mcg of selenium present as 9.8 mcg of selenious acid, nitric acid for pH adjustment (1.8 to 2.4), and water for injection q.s.

Selenious Acid Injection 60 mcg/mL contains no more than 2,500 mcg/L of aluminum and has a calculated osmolarity of 16 mOsmol/L.

Selenious Acid Injection 6 mcg/mL contains no more than 900 mcg/L of aluminum and has a calculated osmolarity of 13 mOsmol/L.

Selenious acid has a molecular weight of 128.97 g/mol and a formula of H2SeO3. The structural formula is:

12 CLINICAL PHARMACOLOGY

12.1 Mechanism of Action

Selenious acid is converted in vivo to hydrogen selenide via glutathione-involved electron reductions. Hydrogen selenide acts as a selenium pool to form selenoproteins which include, but are not limited to, glutathione peroxidase, iodothyronine deiodinase, peroxidase and thioredoxins.

12.2 Pharmacodynamics

Selenious acid exposure-response relationships and the time course of pharmacodynamic responses is unknown.

12.3 Pharmacokinetics

Distribution

In humans 85% of intravenous administered ^75Se-sodium selenite was protein-bound within 4 to 6 hours and 95% by 24 hours.

Elimination

Selenium is primarily eliminated in urine.

16 HOW SUPPLIED

Selenious Acid Injection, USP is a clear, colorless solution available as:

- 600 mcg/10mL (60 mcg/mL) of selenium in a 10 mL pharmacy bulk package. Carton of 5 vials (NDC 0517-6560-05).
- 12 mcg/2 mL (6 mcg/mL) of selenium in a 2 mL single-dose vial. Carton of 10 vials (NDC 0517-6502-10).

The vial closure for both presentation is not made with natural rubber latex.

Store at 20°C to 25°C (68°F to 77°F) [see USP Controlled Room Temperature]

For storage of admixed solution, see Dosage and Administration (2.3).

17 PATIENT COUNSELING INFORMATION

Inform patients, caregivers or home healthcare providers of the following risks of Selenious Acid Injection:

- Pulmonary embolism due to pulmonary vascular precipitates [see Warnings and Precautions (5.1)]
- Vein damage and thrombosis [see Warnings and Precautions (5.2)]
- Aluminum toxicity [see Warnings and Precautions (5.3)]

AMERICAN
REGENT, INC.
SHIRLEY, NY 11967
IN6560
Rev. 8/2021

PRINCIPAL DISPLAY PANEL - Container Label (10 mL)

NDC 0517-6560-01

Rx Only

Selenious Acid Injection, USP

600 mcg*/10 mL
(60 mcg*/mL) of selenium
For intravenous use after dilution and admixing
PRESERVATIVE FREE
10 mL PHARMACY BULK PACKAGE

PRINICIPAL DISPLAY PANEL - Carton Labeling (10 mL)

NDC 0517-6560-05
Rx Only
Selenious Acid Injection, USP
600 mcg*/10 mL
(60 mcg*/mL) of selenium
For intravenous use after dilution and admixing
STERILE. PRESERVATIVE FREE.
25 x 10 mL VIALS
PHARMACY BULK PACKAGE
AMERICAN REGENT, INC.
SHIRLEY, NY 11967

PRINCIPAL DISPLAY PANEL - Container Label (2 mL)

NDC 0517-6502-01

Rx Only

Selenious Acid Injection, USP

12 mcg*/2 mL

(6 mcg*/mL) of selenium
For intravenous use after dilution and admixing
2 mL Single-Dose Vial

PRINCIPAL DISPLAY PANEL - Carton Labeling (2 mL)

NDC 0517-6502-10
Rx Only
Selenious Acid Injection, USP
12 mcg*/2 mL

(6 mcg*/mL) of selenium
For intravenous use after dilution and admixing
PRESERVATIVE FREE
10 X 2 mL Single-Dose Vials